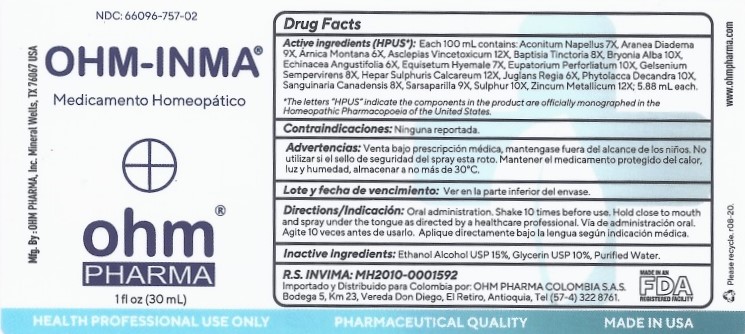 DRUG LABEL: OHM-INMA
NDC: 66096-757 | Form: SPRAY
Manufacturer: OHM PHARMA INC.
Category: homeopathic | Type: HUMAN PRESCRIPTION DRUG LABEL
Date: 20210325

ACTIVE INGREDIENTS: ACONITUM NAPELLUS 7 [hp_X]/30 mL; ARANEUS DIADEMATUS 9 [hp_X]/30 mL; ARNICA MONTANA 6 [hp_X]/30 mL; CYNANCHUM VINCETOXICUM ROOT 12 [hp_X]/30 mL; BAPTISIA TINCTORIA 8 [hp_X]/30 mL; BRYONIA ALBA ROOT 10 [hp_X]/30 mL; ECHINACEA ANGUSTIFOLIA 6 [hp_X]/30 mL; EQUISETUM HYEMALE 7 [hp_X]/30 mL; EUPATORIUM PERFOLIATUM FLOWERING TOP 10 [hp_X]/30 mL; GELSEMIUM SEMPERVIRENS ROOT 8 [hp_X]/30 mL; CALCIUM SULFIDE 12 [hp_X]/30 mL; JUGLANS REGIA LEAF 6 [hp_X]/30 mL; PHYTOLACCA AMERICANA ROOT 10 [hp_X]/30 mL; SANGUINARIA CANADENSIS ROOT 8 [hp_X]/30 mL; SARSAPARILLA 9 [hp_X]/30 mL; SULFUR 10 [hp_X]/30 mL; ZINC 12 [hp_X]/30 mL
INACTIVE INGREDIENTS: ALCOHOL; WATER; GLYCERIN

OHM-INMA

ACTIVE INGREDIENT

ACTIVE INGREDIENTS (HPUS): 100 ml contains: Aconitum Napellus 7X, Aranea Diadema 9X, Arnica Montana 6X, Asclepias Vincetoxicum 12X, Baptisia Tinctoria 8X, Bryonia Alba 10X, Echinacea Angustifolia 6X, Equisetum Hyemale 7x, Eupatorium Perforliatum 10X, Gelsenium Sempervirens 8X, Hepar Sulphuris Calcareum 12X, Juglans Regia 6X, Phytolacca Decandra 10X, Sanguinaria Canadensis 8X, Sarsaparilla 9X, Sulphur 10X, Zincum Metallicum 12X; 5.88 mL each.

*The letters "HPUS" indicate the components in the product are officially monographed in the Homeopathic Pharmacopoeia of the United States.

INDICATIONS AND USAGE

Contraindicaciones: Ninguna reportada

WARNINGS

Advertencias: Venta bajo prescripción médica, mantengase fuera del alcance de los niños. No utilizar si el sello de seguridad del spray esta roto. Mantener el medicamento protegido del calor, luz y humedad, almacenar a no más de 30°C.

KEEP OUT OF REACH OF CHILDREN

Mantengase fuera del alcance de los niños.

DOSAGE AND ADMINISTRATION

Directions / Indicacion: Oral administration. Shake 10 times before use. Hold close to mouth and spray under the tongue as directed by a healthcare professional. Via de administracion oral. Agite 10 veces antes de usarlo. Aplique directamente bajo la lengua segun indicacion medica.

OTHER SAFETY INFORMATION

Lote y fecha de vencimiento:Ver en la parte inferior del envase

INACTIVE INGREDIENT

Inactive ingredients: Ethanol Alcohol USP 15%, Glycerin USP 10%, Purified Water.

QUESTIONS

R.S. INVIMA: MH2010-0001591
Importado y Distribuido para Colombia por: OHM PHARMA COLOMBIA S.A.S.
Bodega 5, Km 23, Vereda Don Diego, El Retiro, Antioquia, Tel (57-4) 322 8761.

Mfg. By : OHM PHARMA, Inc.
Mineral Wells, TX 76067 USA
www.ohmpharma.com

PACKAGE LABEL

NDC: 66096-757-02

OHM-INMA

Medicamento Homeopatico

PURPOSE

Medicamento Homeopatico